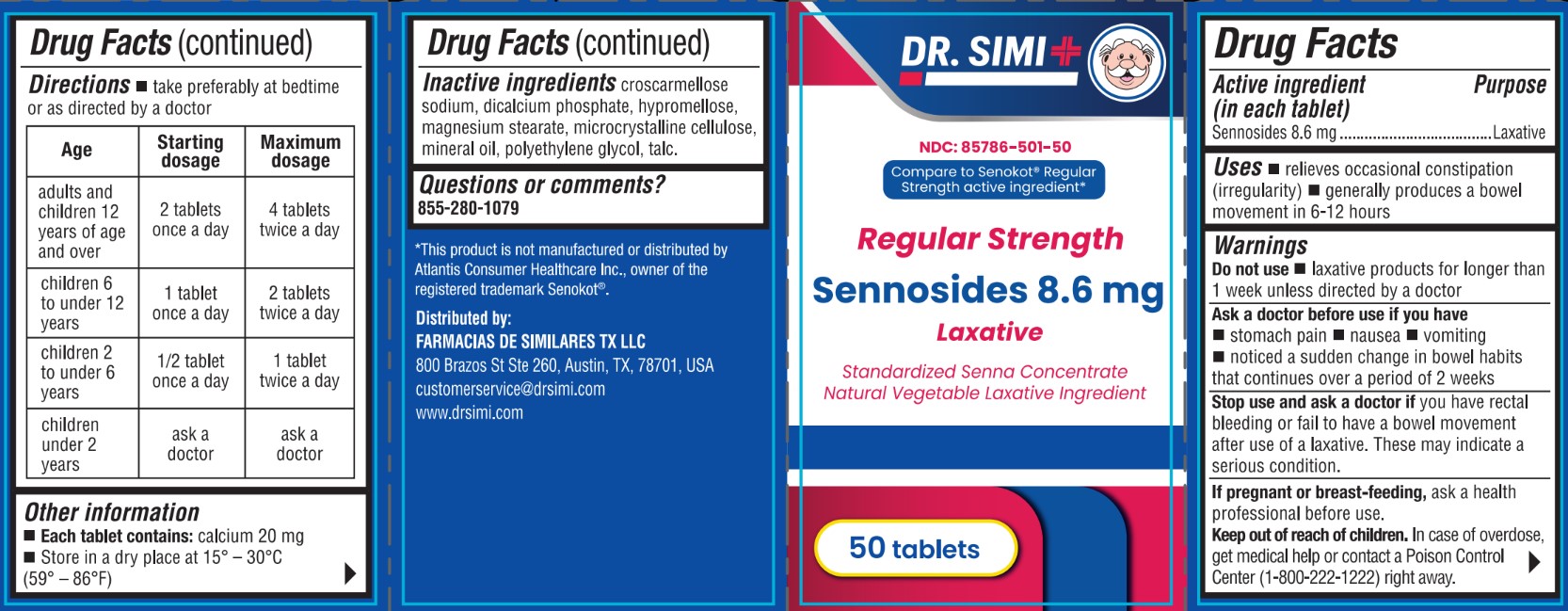 DRUG LABEL: Dr Simi Regular Strength Sennosides 8.6mg
NDC: 85786-501 | Form: TABLET, COATED
Manufacturer: Farmacias De Similares TX LLC
Category: otc | Type: HUMAN OTC DRUG LABEL
Date: 20260121

ACTIVE INGREDIENTS: SENNOSIDES 8.6 mg/1 1
INACTIVE INGREDIENTS: CELLULOSE, MICROCRYSTALLINE; MALTODEXTRIN; LIGHT MINERAL OIL; TALC; CROSCARMELLOSE SODIUM; HYPROMELLOSES; DIBASIC CALCIUM PHOSPHATE DIHYDRATE; MAGNESIUM STEARATE; POLYETHYLENE GLYCOL 400

Active ingredient (in each tablet)

Sennosides 8.6 mg

Purpose

Laxative

Uses

- relieves occasional constipation (irregularity)

- generally produces a bowel movement in 6-12 hours

Warnings

Do not use

- laxative products for longer than 1 week unless directed by a doctor

Ask a doctor before use if you have

- stomach pain

- nausea

- vomiting
-noticed a sudden change in bowel habits that continues over a period of 2 weeks

Stop use and ask a doctor if

you have rectal bleeding or fail to have a bowel movement after use of a laxative. These may indicate a serious condition.

If pregnant or breast-feeding

ask a health professional before use.

Keep out of reach of children.

In case of overdose

get medical help or contact a Poison Control Center (1-800-222-1222) right away.

Directions

- take preferably at bedtime or as directed by a doctor.

Age | Starting Dosage | Maximum Dosage
adults and children 12 years of age and over | 2 tablets once a day | 4 tablets twice a day
children 6 to under 12 years | 1 tablet once a day | 2 tablets twice a day
children 2 to under 6 years | 1/2 tablet once a day | 1 tablet twice a day
children under 2 years | ask a doctor | ask a doctor

Other information

- Each tablet contains: calcium 20 mg
- Store in a dry place at 15° - 30C (59° - 86°F)

Inactive ingredients

croscarmellose sodium, dicalcium phosphate, hypromellose, magnesium stearate, microcrystalline cellulose, mineral oil, polyethylene glycol, talc.

Questions or comments?

855-280-1079

*This product is not manufactured or distributed by Atlantis Consumer Healthcare Inc., owner of the registered trademark Senokot®.

Distributed by:
FARMACIAS DE SIMILARES TX LLC
800 Brazos St Ste 260, Austin, TX, 78701, USA
customerservice@drsimi.com
www.drsimi.com

PACKAGE LABEL

Dr. Simi

NDC: 85786-501-50

Compare to Senokot® Regular Strength active ingredient*

Regular Strength

Sennosides 8.6 mg
Laxative

Standardized Senna Concentrate Natural Vegetable Laxative Ingredient

50 tablets